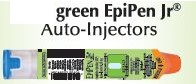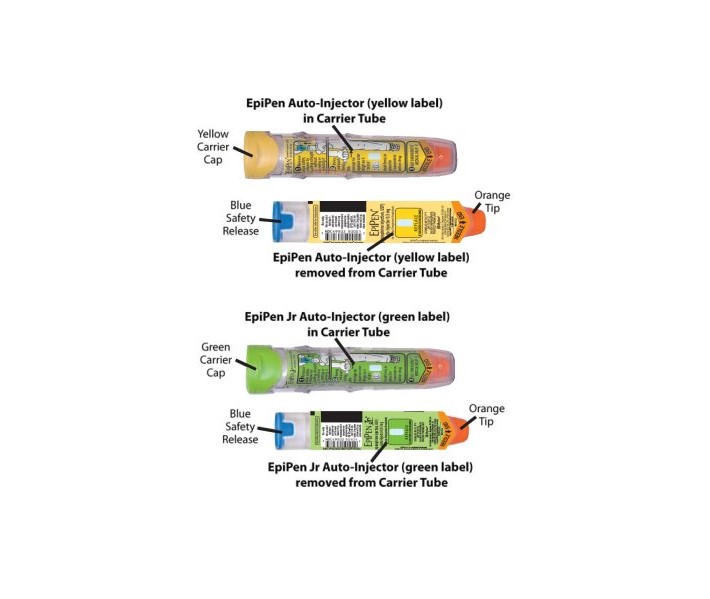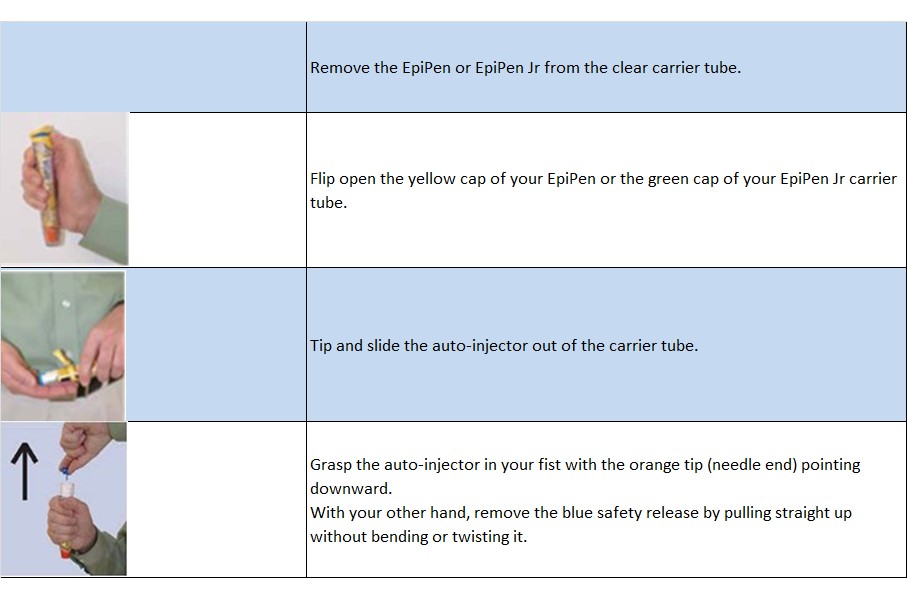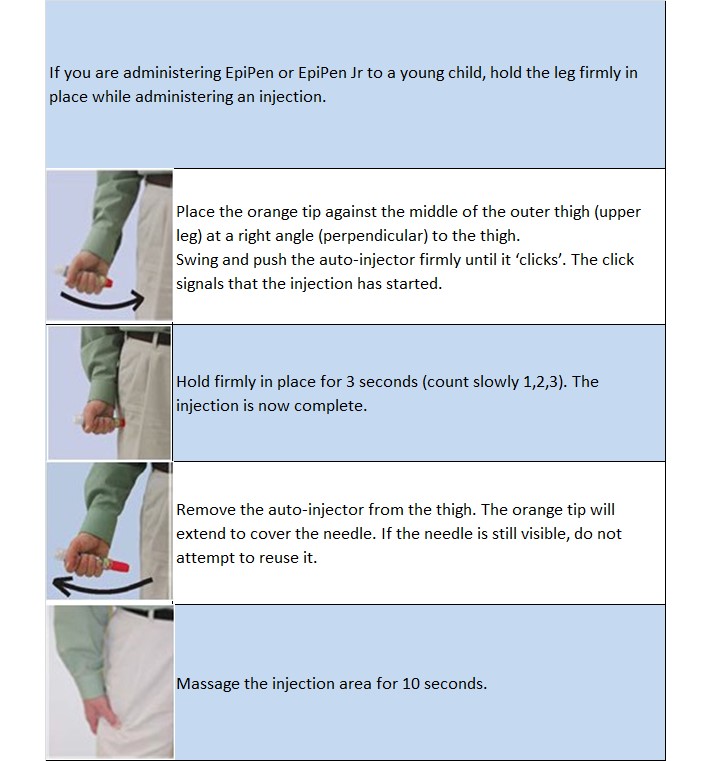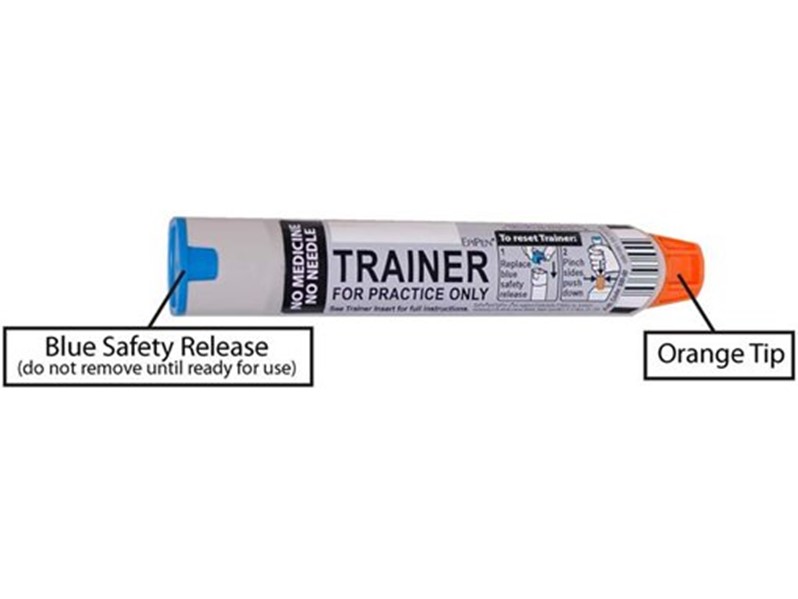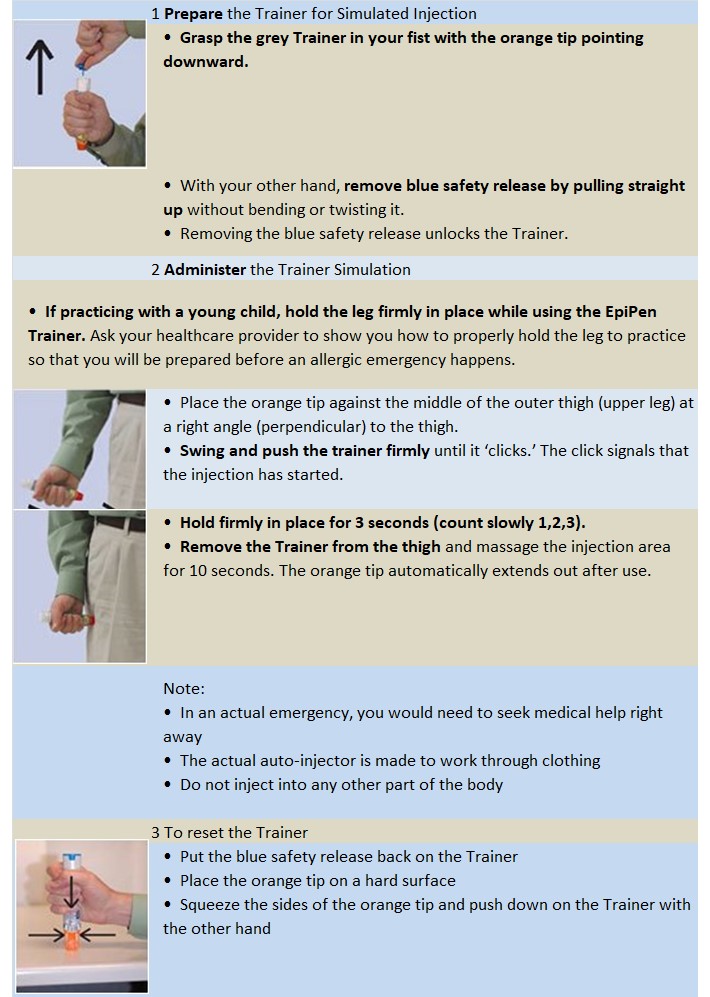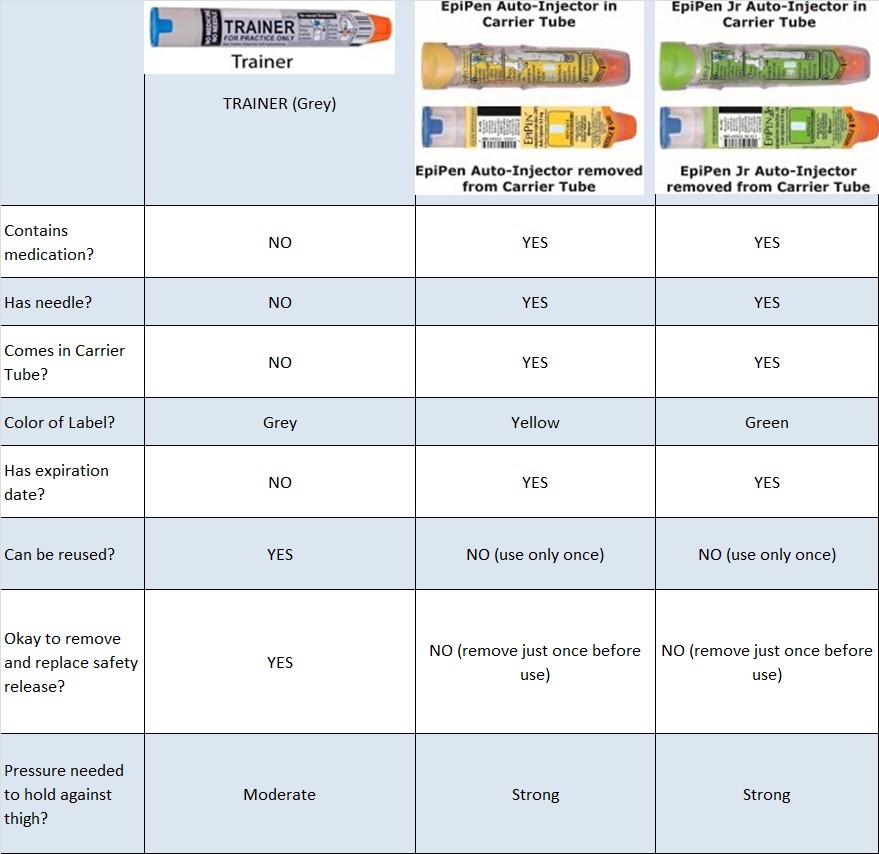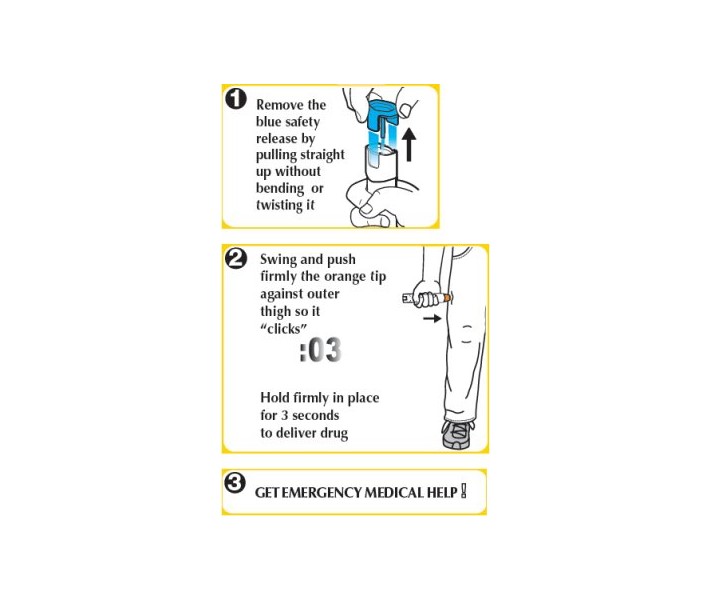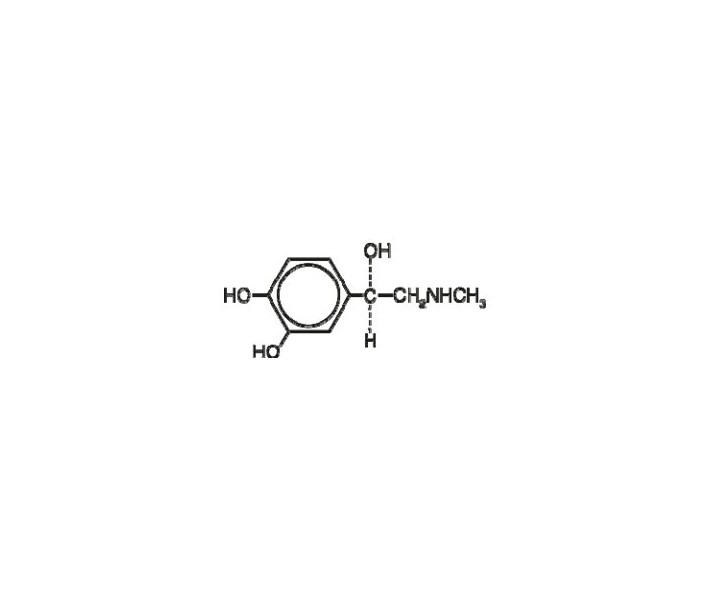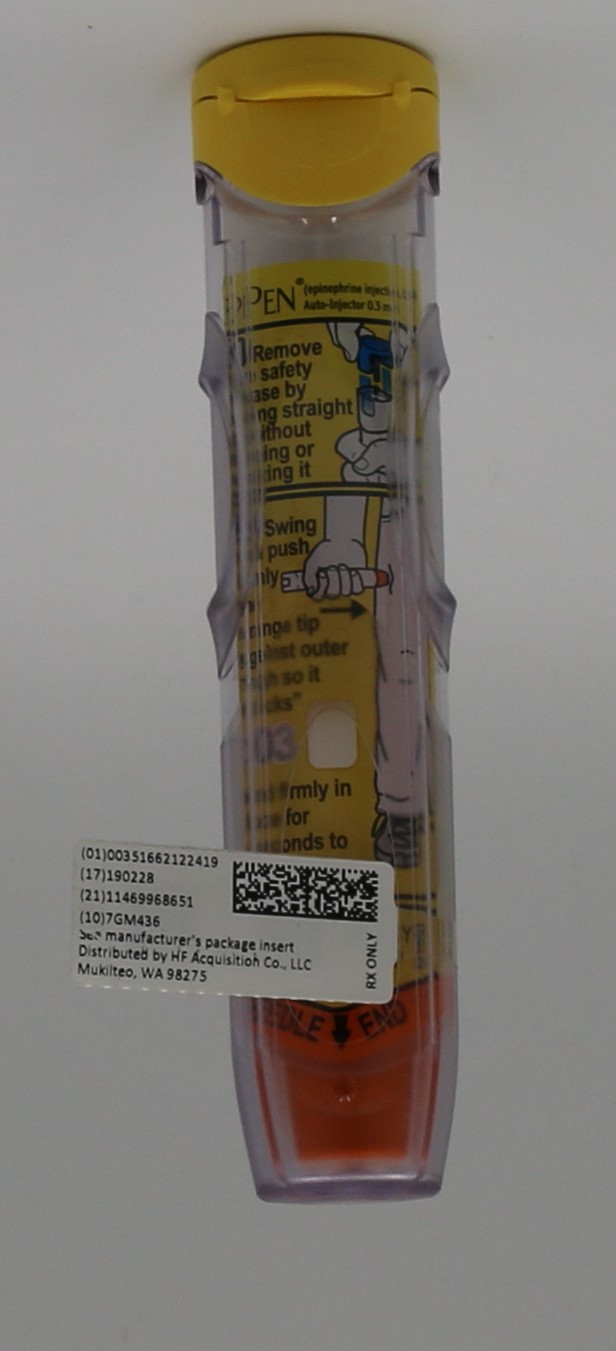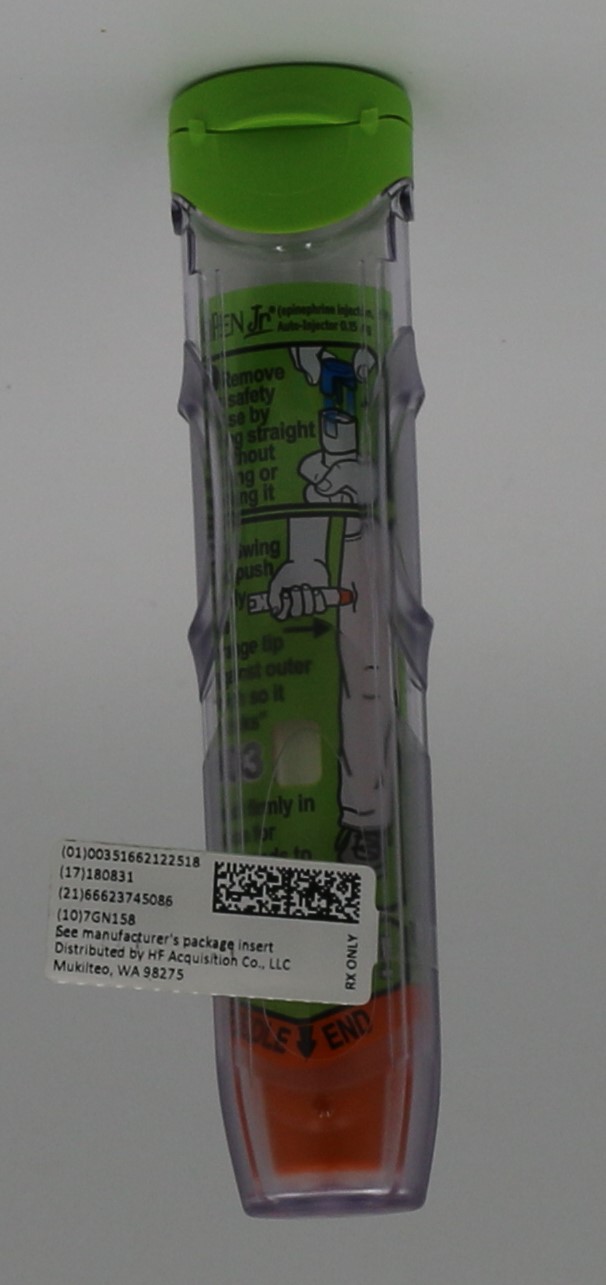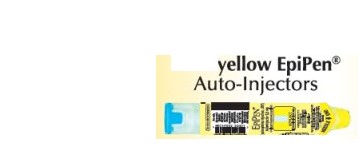 DRUG LABEL: EPINEPHRINE
NDC: 51662-1225 | Form: INJECTION
Manufacturer: HF Acquisition Co LLC, DBA HealthFirst
Category: prescription | Type: HUMAN PRESCRIPTION DRUG LABEL
Date: 20221209

ACTIVE INGREDIENTS: EPINEPHRINE 0.15 mg/0.3 mL
INACTIVE INGREDIENTS: HYDROCHLORIC ACID; WATER; SODIUM CHLORIDE; SODIUM METABISULFITE

EPINEPHRINE INJECTION, USP AUTO INJECTOR

HIGHLIGHTS OF PRESCRIBING INFORMATION

These highlights do not include all the information needed to use EPIPEN ® and EPIPEN Jr ® safely and effectively. See full prescribing information for EPIPEN and EPIPEN Jr.
EPIPEN ® (epinephrine injection, USP), Auto-Injector 0.3 mg, EPIPEN Jr ® (epinephrine injection, USP) Auto-Injector 0.15 mg, for intramuscular or subcutaneous use
Initial U.S. Approval: 1939

INDICATIONS AND USAGE

EpiPen and EpiPen Jr contain epinephrine, a non-selective alpha and beta-adrenergic receptor agonist, indicated in the emergency treatment of allergic reactions (Type I) including anaphylaxis. (1)

DOSAGE AND ADMINISTRATION

• Patients greater than or equal to 30 kg (66 lbs): EpiPen 0.3 mg (2)
• Patients 15 to 30 kg (33 lbs to 66 lbs): EpiPen Jr 0.15 mg (2)

Inject EpiPen and EpiPen Jr intramuscularly or subcutaneously into the anterolateral aspect of the thigh, through clothing if necessary. Each device is a single-use injection. (2)

DOSAGE FORMS AND STRENGTHS

• EpiPen: Injection, 0.3 mg: 0.3 mg/0.3 mL epinephrine, USP, pre-filled auto-injector (3)
• EpiPen Jr: Injection, 0.15 mg: 0.15 mg/0.3 mL epinephrine, USP, pre-filled auto-injector (3)

CONTRAINDICATIONS

None (4)

WARNINGS AND PRECAUTIONS

• In conjunction with use, seek immediate medical or hospital care. 5 (5.1)
• Do not inject intravenously, into buttock, or into digits, hands, or feet. 5 (5.2)
• To minimize the risk of injection related injury, instruct caregivers to hold the child’s leg firmly in place and limit movement prior to and during injection when administering to young children. 5 (5.2)
• Rare cases of serious skin and soft tissue infections have been reported following epinephrine injection. Advise patients to seek medical care if they develop signs or symptoms of infection. 5 (5.3)
• The presence of a sulfite in this product should not deter use. 5 (5.4)
• Administer with caution in patients with heart disease; may aggravate angina pectoris or produce ventricular arrhythmias. 5 (5.5)

ADVERSE REACTIONS

Adverse reactions to epinephrine include anxiety, apprehensiveness, restlessness, tremor, weakness, dizziness, sweating, palpitations, pallor, nausea and vomiting, headache, and/or respiratory difficulties. 6 (6)

To report SUSPECTED ADVERSE REACTIONS, contact Mylan at 1-877-446-3679 (1-877-4-INFO-RX) or FDA at 1-800-FDA-1088 or www.fda.gov/medwatch.

DRUG INTERACTIONS

• Cardiac glycosides or diuretics: observe for development of cardiac arrhythmias. 7 (7)
• Tricyclic antidepressants, monoamine oxidase inhibitors, levothyroxine sodium, and certain antihistamines: potentiate effects of epinephrine. 7 (7)
• Beta-adrenergic blocking drugs: antagonize cardiostimulating and bronchodilating effects of epinephrine. 7 (7)
• Alpha-adrenergic blocking drugs: antagonize vasoconstricting and hypertensive effects of epinephrine. 7 (7)
• Ergot alkaloids: may reverse the pressor effects of epinephrine. 7 (7)

USE IN SPECIFIC POPULATIONS

• Elderly patients may be at greater risk of developing adverse reactions. 5 (5.5), 8 (8.5)

See 17 for PATIENT COUNSELING INFORMATION and FDA-approved patient labeling.

Revised: 8/2018

FULL PRESCRIBING INFORMATION: CONTENTS*

1 INDICATIONS AND USAGE
2 DOSAGE AND ADMINISTRATION
3 DOSAGE FORMS AND STRENGTHS
4 CONTRAINDICATIONS
5 WARNINGS AND PRECAUTIONS
5.1 Emergency Treatment
5.2 Injection-Related Complications
5.3 Serious Infections at the Injection Site
5.4 Allergic Reactions Associated with Sulfite
5.5 Disease Interactions
6 ADVERSE REACTIONS
7 DRUG INTERACTIONS
8 USE IN SPECIFIC POPULATIONS
8.1 Pregnancy
8.2 Lactation
8.4 Pediatric Use
8.5 Geriatric Use
10 OVERDOSAGE
11 DESCRIPTION
12 CLINICAL PHARMACOLOGY
12.1 Mechanism of Action
12.2 Pharmacodynamics
13 NONCLINICAL TOXICOLOGY
13.1 Carcinogenesis, Mutagenesis, Impairment of Fertility
16 HOW SUPPLIED/STORAGE AND HANDLING
16.1 How Supplied
16.2 Storage and Handling
17 PATIENT COUNSELING INFORMATION

* Sections or subsections omitted from the full prescribing information are not listed.

Close

1 INDICATIONS & USAGE

EpiPen and EpiPen Jr are indicated in the emergency treatment of allergic reactions (Type I) including anaphylaxis to stinging insects (e.g., order Hymenoptera, which include bees, wasps, hornets, yellow jackets and fire ants) and biting insects (e.g., triatoma, mosquitoes), allergen immunotherapy, foods, drugs, diagnostic testing substances (e.g., radiocontrast media) and other allergens, as well as idiopathic anaphylaxis or exercise-induced anaphylaxis.

EpiPen and EpiPen Jr are intended for immediate administration in patients who are determined to be at increased risk for anaphylaxis, including individuals with a history of anaphylactic reactions.

Anaphylactic reactions may occur within minutes after exposure and consist of flushing, apprehension, syncope, tachycardia, thready or unobtainable pulse associated with a fall in blood pressure, convulsions, vomiting, diarrhea and abdominal cramps, involuntary voiding, wheezing, dyspnea due to laryngeal spasm, pruritus, rashes, urticaria or angioedema.

EpiPen and EpiPen Jr are intended for immediate administration as emergency supportive therapy only and are not a substitute for immediate medical care.

2 DOSAGE & ADMINISTRATION

Selection of the appropriate dosage strength (EpiPen 0.3 mg or EpiPen Jr 0.15 mg) is determined according to patient body weight.

•
Patients greater than or equal to 30 kg (approximately 66 pounds or more): EpiPen 0.3 mg
•
Patients 15 to 30 kg (33 pounds to 66 pounds): EpiPen Jr 0.15 mg

Inject EpiPen or EpiPen Jr intramuscularly or subcutaneously into the anterolateral aspect of the thigh, through clothing if necessary. Instruct caregivers of young children who are prescribed an EpiPen or EpiPen Jr and who may be uncooperative and kick or move during an injection to hold the leg firmly in place and limit movement prior to and during an injection [see WARNINGS AND PRECAUTIONS (5.2)].

Each EpiPen or EpiPen Jr contains a single dose of epinephrine for single-use injection. Since the doses of epinephrine delivered from EpiPen or EpiPen Jr are fixed, consider using other forms of injectable epinephrine if doses lower than 0.15 mg are deemed necessary.

The prescriber should carefully assess each patient to determine the most appropriate dose of epinephrine, recognizing the life-threatening nature of the reactions for which this drug is indicated. With severe persistent anaphylaxis, repeat injections with an additional EpiPen or EpiPen Jr may be necessary. More than two sequential doses of epinephrine should only be administered under direct medical supervision [see WARNINGS AND PRECAUTIONS (5.1)].

The epinephrine solution in the clear window of the EpiPen Auto-Injector should be inspected visually for particulate matter and discoloration. Epinephrine is light sensitive and should be stored in the carrier tube provided to protect it from light [see HOW SUPPLIED/STORAGE AND HANDLING (16.2)].

3 DOSAGE FORMS & STRENGTHS

• EpiPen: Injection, 0.3 mg/0.3 mL epinephrine injection, USP, pre-filled auto-injector
• EpiPen Jr: Injection, 0.15 mg/0.3 mL, epinephrine injection, USP, pre-filled auto-injector

4 CONTRAINDICATIONS

None

5 WARNINGS AND PRECAUTIONS

5.1 Emergency Treatment

EpiPen and EpiPen Jr are intended for immediate administration as emergency supportive therapy and are not intended as a substitute for immediate medical care. In conjunction with the administration of epinephrine, the patient should seek immediate medical or hospital care. More than two sequential doses of epinephrine should only be administered under direct medical supervision [see INDICATIONS & USAGE (1), DOSAGE & ADMINISTRATION (2) and PATIENT COUNSELING INFORMATION (17)].

5.2 Injection-Related Complications

EpiPen and EpiPen Jr should only be injected into the anterolateral aspect of the thigh [see DOSAGE & ADMINISTRATION (2) and PATIENT COUNSELING INFORMATION (17)].

• Do not inject intravenously. Large doses or accidental intravenous injection of epinephrine may result in cerebral hemorrhage due to sharp rise in blood pressure. Rapidly acting vasodilators can counteract the marked pressor effects of epinephrine if there is such inadvertent administration.
• Do not inject into buttock. Injection into the buttock may not provide effective treatment of anaphylaxis. Advise the patient to go immediately to the nearest emergency room for further treatment of anaphylaxis. Additionally, injection into the buttock has been associated with Clostridial infections (gas gangrene). Cleansing with alcohol does not kill bacterial spores, and therefore, does not lower this risk.
• Do not inject into digits, hands or feet. Since epinephrine is a strong vasoconstrictor, accidental injection into the digits, hands or feet may result in loss of blood flow to the affected area. Advise the patient to go immediately to the nearest emergency room and to inform the healthcare provider in the emergency room of the location of the accidental injection. Treatment of such inadvertent administration should consist of vasodilation, in addition to further appropriate treatment of anaphylaxis [ see ADVERSE REACTIONS (6)].
• Hold leg firmly during injection. Lacerations, bent needles, and embedded needles have been reported when EpiPen and EpiPen Jr have been injected into the thigh of young children who are uncooperative and kick or move during an injection. To minimize the risk of injection related injury when administering EpiPen to young children, instruct caregivers to hold the child’s leg firmly in place and limit movement prior to and during injection.

5.3 Serious Infections at the Injection Site

Rare cases of serious skin and soft tissue infections, including necrotizing fasciitis and myonecrosis caused by Clostridia (gas gangrene), have been reported at the injection site following epinephrine injection for anaphylaxis. Clostridium spores can be present on the skin and introduced into the deep tissue with subcutaneous or intramuscular injection. While cleansing with alcohol may reduce presence of bacteria on the skin, alcohol cleansing does not kill Clostridium spores. To decrease the risk of Clostridium infection, do not inject EpiPen into the buttock [see WARNINGS AND PRECAUTIONS (5.2)]. Advise patients to seek medical care if they develop signs or symptoms of infection, such as persistent redness, warmth, swelling, or tenderness, at the epinephrine injection site.

5.4 Allergic Reactions Associated with Sulfite

The presence of a sulfite in this product should not deter administration of the drug for treatment of serious allergic or other emergency situations even if the patient is sulfite-sensitive.

Epinephrine is the preferred treatment for serious allergic reactions or other emergency situations even though this product contains sodium metabisulfite, a sulfite that may, in other products, cause allergic-type reactions including anaphylactic symptoms or life-threatening or less severe asthmatic episodes in certain susceptible persons.

The alternatives to using epinephrine in a life-threatening situation may not be satisfactory.

5.5 Disease Interactions

Some patients may be at greater risk for developing adverse reactions after epinephrine administration. Despite these concerns, it should be recognized that the presence of these conditions is not a contraindication to epinephrine administration in an acute, life-threatening situation. Therefore, patients with these conditions, and/or any other person who might be in a position to administer EpiPen or EpiPen Jr to a patient experiencing anaphylaxis should be carefully instructed in regard to the circumstances under which epinephrine should be used.

• Patients with Heart Disease

Epinephrine should be administered with caution to patients who have heart disease, including patients with cardiac arrhythmias, coronary artery or organic heart disease, or hypertension. In such patients, or in patients who are on drugs that may sensitize the heart to arrhythmias, epinephrine may precipitate or aggravate angina pectoris as well as produce ventricular arrhythmias [see DRUG INTERACTIONS (7) and ADVERSE REACTIONS (6)].

• Other Patients and Diseases

Epinephrine should be administered with caution to patients with hyperthyroidism, diabetes, elderly individuals, and pregnant women. Patients with Parkinson’s disease may notice a temporary worsening of symptoms.

6 ADVERSE REACTIONS

Due to the lack of randomized, controlled clinical trials of epinephrine for the treatment of anaphylaxis, the true incidence of adverse reactions associated with the systemic use of epinephrine is difficult to determine. Adverse reactions reported in observational trials, case reports, and studies are listed below.

Common adverse reactions to systemically administered epinephrine include anxiety; apprehensiveness; restlessness; tremor; weakness; dizziness; sweating; palpitations; pallor; nausea and vomiting; headache; and/or respiratory difficulties. These symptoms occur in some persons receiving therapeutic doses of epinephrine, but are more likely to occur in patients with hypertension or hyperthyroidism [see WARNINGS AND PRECAUTIONS (5.5)].

Arrhythmias, including fatal ventricular fibrillation, have been reported, particularly in patients with underlying cardiac disease or those receiving certain drugs [see WARNINGS AND PRECAUTIONS (5.5) and DRUG INTERACTIONS (7)].

Rapid rises in blood pressure have produced cerebral hemorrhage, particularly in elderly patients with cardiovascular disease [see WARNINGS AND PRECAUTIONS (5.5)].

Angina may occur in patients with coronary artery disease [see WARNINGS AND PRECAUTIONS (5.5)].

Rare cases of stress cardiomyopathy have been reported in patients treated with epinephrine.

Accidental injection into the digits, hands or feet may result in loss of blood flow to the affected area [see WARNINGS AND PRECAUTIONS (5.2)].

Adverse events experienced as a result of accidental injections may include increased heart rate, local reactions including injection site pallor, coldness and hypoesthesia or injury at the injection site resulting in bruising, bleeding, discoloration, erythema or skeletal injury.

Lacerations, bent needles, and embedded needles have been reported when EpiPen has been injected into the thigh of young children who are uncooperative and kick or move during the injection [see WARNINGS AND PRECAUTIONS (5.2)].

Injection into the buttock has resulted in cases of gas gangrene [see WARNINGS AND PRECAUTIONS (5.2)].

Rare cases of serious skin and soft tissue infections, including necrotizing fasciitis and myonecrosis caused by Clostridia (gas gangrene), have been reported following epinephrine injection, including EpiPen, in the thigh [see WARNINGS AND PRECAUTIONS (5.3)].

7 DRUG INTERACTIONS

Patients who receive epinephrine while concomitantly taking cardiac glycosides, diuretics, or anti-arrhythmics should be observed carefully for the development of cardiac arrhythmias [see WARNINGS AND PRECAUTIONS (5.5)].

The effects of epinephrine may be potentiated by tricyclic antidepressants, monoamine oxidase inhibitors, levothyroxine sodium, and certain antihistamines, notably chlorpheniramine, tripelennamine, and diphenhydramine.

The cardiostimulating and bronchodilating effects of epinephrine are antagonized by beta- adrenergic blocking drugs, such as propranolol.

The vasoconstricting and hypertensive effects of epinephrine are antagonized by alpha- adrenergic blocking drugs, such as phentolamine.

Ergot alkaloids may also reverse the pressor effects of epinephrine.

8 USE IN SPECIFIC POPULATIONS

8.1 Pregnancy

Risk Summary

There are no adequate and well controlled studies of the acute effect of epinephrine in pregnant women. In animal reproductive studies, epinephrine administered by the subcutaneous route to rabbits, mice, and hamsters during the period of organogenesis was teratogenic at doses 7 times and higher than the maximum recommended human intramuscular and subcutaneous dose on a mg/m2 basis. Epinephrine is the first-line medication of choice for the treatment of anaphylaxis during pregnancy in humans. Epinephrine should be used for treatment of anaphylaxis during pregnancy in the same manner as it is used in non-pregnant patients.

In the U.S. general population, the estimated background risk of major birth defects and miscarriage in clinically recognized pregnancies is 2 to 4% and 15 to 20%, respectively.

Clinical Considerations

Disease-associated maternal and embryo/fetal risk

During pregnancy, anaphylaxis can be catastrophic and can lead to hypoxic-ischemic encephalopathy and permanent central nervous system damage or death in the mother and, more commonly, in the fetus or neonate. The prevalence of anaphylaxis occurring during pregnancy is reported to be approximately 3 cases per 100,000 deliveries.

Management of anaphylaxis during pregnancy is similar to management in the general population. Epinephrine is the first line-medication of choice for treatment of anaphylaxis; it should be used in the same manner in pregnant and non-pregnant patients. In conjunction with the administration of epinephrine, the patient should seek immediate medical or hospital care.

Data

Animal Data

In an embryofetal development study with rabbits dosed during the period of organogenesis, epinephrine was shown to be teratogenic (including gastroschisis and embryonic lethality) at doses approximately 40 times the maximum recommended intramuscular or subcutaneous dose (on a mg/m2 basis at a maternal subcutaneous dose of 1.2 mg/kg/day for two to three days).

In an embryofetal development study with mice dosed during the period of organogenesis, epinephrine was shown to be teratogenic (including embryonic lethality) at doses approximately 8 times the maximum recommended intramuscular or subcutaneous dose (on a mg/m2 basis at maternal subcutaneous dose of 1 mg/kg/day for 10 days). These effects were not seen in mice at approximately 4 times the maximum recommended daily intramuscular or subcutaneous dose (on a mg/m2 basis at a subcutaneous maternal dose of 0.5 mg/kg/day for 10 days).

In an embryofetal development study with hamsters dosed during the period of organogenesis from gestation days 7 to 10, epinephrine was shown to be teratogenic at doses approximately 7 times the maximum recommended intramuscular or subcutaneous dose (on a mg/m2 basis at a maternal subcutaneous dose of 0.5 mg/kg/day).

8.2 Lactation

Risk Summary

There is no information on the presence of epinephrine in human milk, the effects on breastfed infants, or the effects on milk production. Epinephrine is the first line-medication of choice for treatment of anaphylaxis; it should be used in the same manner in breastfeeding and non-breastfeeding patients.

8.4 Pediatric Use

EpiPen or EpiPen Jr may be administered to pediatric patients at a dosage appropriate to body weight [see DOSAGE & ADMINISTRATION (2)]. Clinical experience with the use of epinephrine suggests that the adverse reactions seen in children are similar in nature and extent to those both expected and reported in adults. Since the doses of epinephrine delivered from EpiPen and EpiPen Jr are fixed, consider using other forms of injectable epinephrine if doses lower than 0.15 mg are deemed necessary.

8.5 Geriatric Use

Clinical studies for the treatment of anaphylaxis have not been performed in subjects aged 65 and over to determine whether they respond differently from younger subjects. However, other reported clinical experience with use of epinephrine for the treatment of anaphylaxis has identified that geriatric patients may be particularly sensitive to the effects of epinephrine. Therefore, EpiPen should be administered with caution in elderly individuals, who may be at greater risk for developing adverse reactions after epinephrine administration [see WARNINGS AND PRECAUTIONS (5.5), OVERDOSAGE (10)].

10 OVERDOSAGE

Overdosage of epinephrine may produce extremely elevated arterial pressure, which may result in cerebrovascular hemorrhage, particularly in elderly patients. Overdosage may also result in pulmonary edema because of peripheral vascular constriction together with cardiac stimulation. Treatment consists of rapidly acting vasodilators or alpha-adrenergic blocking drugs and/or respiratory support.

Epinephrine overdosage can also cause transient bradycardia followed by tachycardia, and these may be accompanied by potentially fatal cardiac arrhythmias. Premature ventricular contractions may appear within one minute after injection and may be followed by multifocal ventricular tachycardia (prefibrillation rhythm). Subsidence of the ventricular effects may be followed by atrial tachycardia and occasionally by atrioventricular block. Treatment of arrhythmias consists of administration of a beta-adrenergic blocking drug such as propranolol.

Overdosage sometimes results in extreme pallor and coldness of the skin, metabolic acidosis, and kidney failure. Suitable corrective measures must be taken in such situations.

11 DESCRIPTION

EpiPen (epinephrine injection, USP) 0.3 mg and EpiPen Jr (epinephrine injection, USP) 0.15 mg are auto-injectors and combination products containing drug and device components.

Each EpiPen Auto-Injector, 0.3 mg delivers a single dose of 0.3 mg epinephrine from epinephrine injection, USP 0.3 mg/0.3 mL in a sterile solution.

Each EpiPen Jr Auto-Injector, 0.15 mg delivers a single dose of 0.15 mg epinephrine from epinephrine injection, USP 0.15 mg/0.3 mL in a sterile solution.

The EpiPen and EpiPen Jr each contain 2 mL epinephrine solution. Approximately 1.7 mL remains in the auto-injector after activation, but is not available for future use, and should be discarded.

Each 0.3 mL in the EpiPen Auto-Injector contains 0.3 mg epinephrine, 1.8 mg sodium chloride, 0.5 mg sodium metabisulfite, hydrochloric acid to adjust pH, and Water for Injection. The pH range is 2.2–5.0.

Each 0.3 mL in the EpiPen Jr Auto-Injector contains 0.15 mg epinephrine, 1.8 mg sodium chloride, 0.5 mg sodium metabisulfite, hydrochloric acid to adjust pH, and Water for Injection. The pH range is 2.2-5.0.

Epinephrine is a sympathomimetic catecholamine. Chemically, epinephrine is (-)-3,4- Dihydroxy-α-[(methylamino)methyl]benzyl alcohol with the following structure:

Epinephrine solution deteriorates rapidly on exposure to air or light, turning pink from oxidation to adrenochrome and brown from the formation of melanin. Replace EpiPen and EpiPen Jr if the epinephrine solution appears discolored (pinkish or brown color), cloudy, or contains particles.

Thoroughly review the patient instructions and operation of EpiPen or EpiPen Jr with patients and caregivers prior to use [see PATIENT COUNSELING INFORMATION (17)].

12 CLINICAL PHARMACOLOGY

12.1 Mechanism of Action

Epinephrine acts on both alpha- and beta-adrenergic receptors.

12.2 Pharmacodynamics

Through its action on alpha-adrenergic receptors, epinephrine lessens the vasodilation and increased vascular permeability that occurs during anaphylaxis, which can lead to loss of intravascular fluid volume and hypotension.

Through its action on beta-adrenergic receptors, epinephrine causes bronchial smooth muscle relaxation and helps alleviate bronchospasm, wheezing and dyspnea that may occur during anaphylaxis.

Epinephrine also alleviates pruritus, urticaria, and angioedema and may relieve gastrointestinal and genitourinary symptoms associated with anaphylaxis because of its relaxer effects on the smooth muscle of the stomach, intestine, uterus and urinary bladder.

When given subcutaneously or intramuscularly, epinephrine has a rapid onset and short duration of action.

13 NONCLINICAL TOXICOLOGY

13.1 Carcinogenesis, Mutagenesis, Impairment of Fertility

Long-term studies to evaluate the carcinogenic potential of epinephrine have not been conducted.

Epinephrine and other catecholamines have been shown to have mutagenic potential in vitro. Epinephrine was positive in the Salmonella bacterial reverse mutation assay, positive in the mouse lymphoma assay, and negative in the in vivo micronucleus assay. Epinephrine is an oxidative mutagen based on the E. coli WP2 Mutoxitest bacterial reverse mutation assay. This should not prevent the use of epinephrine under the conditions noted under INDICATIONS & USAGE (1).

The potential for epinephrine to impair reproductive performance has not been evaluated, but epinephrine has been shown to decrease implantation in female rabbits dosed subcutaneously with 1.2 mg/kg/day (40-fold the highest human intramuscular or subcutaneous daily dose) during gestation days 3 to 9.

16 HOW SUPPLIED/STORAGE & HANDLING

EPIPEN® (EPINEPHRINE INJECTION, USP) is supplied in the following dosage forms.
NDC 51662-1224-1
EPIPEN® (EPINEPHRINE INJECTION, USP) AUTO INJECTOR 0.30mg

NDC 51662-1225-1
EPIPEN JR® (EPINEPHRINE INJECTION, USP) AUTO INJECTOR 0.15mg

HF Acquisition Co LLC, DBA HealthFirst
Mukilteo, WA 98275

Also supplied in the following manufacture supplied dosage forms

16.1 How Supplied

EpiPen Auto-Injectors (epinephrine injections, USP 0.3 mg/0.3 mL) are available as EpiPen 2-Pak®, NDC 49502-500-02, a pack that contains two EpiPen Auto-Injectors (epinephrine injections, USP 0.3 mg/0.3 mL) and one EpiPen Auto-Injector trainer device.

EpiPen Jr Auto-Injectors (epinephrine injections, USP 0.15 mg/0.3 mL) are available as EpiPen Jr 2-Pak®, NDC 49502-501-02, a pack that contains two EpiPen Jr Auto-Injectors (epinephrine injections, USP 0.15 mg/0.3 mL) and one EpiPen Auto-Injector trainer device.

EpiPen 2-Pak® and EpiPen Jr 2-Pak® also include an S-clip to clip two carrier tubes together.

Rx only

16.2 Storage and Handling

Protect from light. Epinephrine is light sensitive and should be stored in the carrier tube provided to protect it from light. Store at 20° to 25°C (68° to 77°F); excursions permitted to 15° to 30°C (59° to 86°F) [See USP Controlled Room Temperature]. Do not refrigerate. Before using, check to make sure the solution in the auto-injector is clear and colorless. Replace the auto-injector if the solution is discolored (pinkish or brown color), cloudy, or contains particles.

17 PATIENT COUNSELING INFORMATION

[See FDA-Approved Patient Labeling (PATIENT INFORMATION AND INSTRUCTIONS FOR USE).]

A healthcare provider should review the patient instructions and operation of EpiPen and EpiPen Jr in detail, with the patient or caregiver.

Epinephrine is essential for the treatment of anaphylaxis. Patients who are at risk of or with a history of severe allergic reactions (anaphylaxis) to insect stings or bites, foods, drugs, and other allergens, as well as idiopathic and exercise-induced anaphylaxis, should be carefully instructed about the circumstances under which epinephrine should be used.

Administration and Training

Instruct patients and/or caregivers in the appropriate use of EpiPen and EpiPen Jr. EpiPen should be injected into the middle of the outer thigh (through clothing, if necessary). Each device is a single-use injection. Advise patients to seek immediate medical care in conjunction with administration of EpiPen.

Instruct caregivers to hold the leg of young children firmly in place and limit movement prior to and during injection. Lacerations, bent needles, and embedded needles have been reported when EpiPen and EpiPen Jr have been injected into the thigh of young children who are uncooperative and kick or move during an injection [see WARNINGS AND PRECAUTIONS (5.2)].

Complete patient information, including dosage, directions for proper administration and precautions can be found inside each EpiPen or EpiPen Jr carton. A printed label on the surface of EpiPen shows instructions for use and a diagram depicting the injection process.

Instruct patients and/or caregivers to use and practice with the Trainer to familiarize themselves with the use of EpiPen in an allergic emergency. The Trainer may be used multiple times. A Trainer device is provided in 2-Pak cartons.

Adverse Reactions

Epinephrine may produce symptoms and signs that include an increase in heart rate, the sensation of a more forceful heartbeat, palpitations, sweating, nausea and vomiting, difficulty breathing, pallor, dizziness, weakness or shakiness, headache, apprehension, nervousness, or anxiety. These signs and symptoms usually subside rapidly, especially with rest, quiet and recumbency. Patients with hypertension or hyperthyroidism may develop more severe or persistent effects, and patients with coronary artery disease could experience angina. Patients with diabetes may develop increased blood glucose levels following epinephrine administration. Patients with Parkinson’s disease may notice a temporary worsening of symptoms [see WARNINGS AND PRECAUTIONS (5.5)].

Accidental Injection

Advise patients to seek immediate medical care in the case of accidental injection. Since epinephrine is a strong vasoconstrictor when injected into the digits, hands, or feet, treatment should be directed at vasodilatation if there is such an accidental injection to these areas [see WARNINGS AND PRECAUTIONS (5.2)].

Serious Infections at the Injection Site

Rare cases of serious skin and soft tissue infections, including necrotizing fasciitis and myonecrosis caused by Clostridia (gas gangrene), have been reported at the injection site following epinephrine injection for anaphylaxis. Advise patients to seek medical care if they develop signs or symptoms of infection, such as persistent redness, warmth, swelling, or tenderness, at the epinephrine injection site [see WARNINGS AND PRECAUTIONS (5.3)].

Storage and Handling

Instruct patients to inspect the epinephrine solution visually through the clear window of the auto-injector periodically. Replace EpiPen and EpiPen Jr if the epinephrine solution appears discolored (pinkish or brown color), cloudy, or contains particles. Epinephrine is light sensitive and should be stored in the carrier tube provided to protect it from light. The carrier tube is not waterproof. Instruct patients that EpiPen and EpiPen Jr must be used or properly disposed once the blue safety release is removed or after use [see STORAGE AND HANDLING (16.2)].

Complete patient information, including dosage, directions for proper administration and precautions can be found inside each EpiPen Auto-Injector carton.

Manufactured for Mylan Specialty L.P., Morgantown, WV 26505, U.S.A. by Meridian Medical Technologies, Inc., Columbia, MD 21046, U.S.A., a Pfizer company

EpiPen® and EpiPen Jr® are registered trademarks of Mylan Inc. licensed exclusively to its wholly-owned affiliate, Mylan Specialty L. P. of Morgantown, WV 26505, U.S.A.

Copyright © 2018 Meridian Medical Technologies. All rights reserved.

Revised: 8/2018
MS:EPI:R4

0002029

PATIENT INFORMATION/INSTRUCTIONS FOR USE

EPIPEN®
(epinephrine injection, USP) Auto-Injector 0.3 mg
EpiPen® = one dose of 0.3 mg epinephrine, USP 0.3 mg/0.3 mL

EPIPEN JR®
(epinephrine injection, USP) Auto-Injector 0.15 mg
EpiPen Jr® = one dose of 0.15 mg epinephrine, USP 0.15 mg/0.3 mL

For allergic emergencies (anaphylaxis)

Patient Information

Read this Patient Information Leaflet carefully before using the EpiPen® or EpiPen Jr® Auto-Injector and each time you get a refill. There may be new information. You, your parent, caregiver, or others who may be in a position to administer EpiPen or EpiPen Jr Auto-Injector, should know how to use it before you have an allergic emergency.

This information does not take the place of talking with your healthcare provider about your medical condition or your treatment.

What is the most important information I should know about the EpiPen and EpiPen Jr?

1.
EpiPen and EpiPen Jr contain epinephrine, a medicine used to treat allergic emergencies (anaphylaxis). Anaphylaxis can be life threatening, can happen within minutes, and can be caused by stinging and biting insects, allergy injections, foods, medicines, exercise, or unknown causes.
Symptoms of anaphylaxis may include:

•
trouble breathing
•
wheezing
•
hoarseness (changes in the way your voice sounds)
•
hives (raised reddened rash that may itch)
•
severe itching
•
swelling of your face, lips, mouth, or tongue
•
skin rash, redness, or swelling
•
fast heartbeat
•
weak pulse
•
feeling very anxious
•
confusion
•
stomach pain
•
losing control of urine or bowel movements (incontinence)
•
diarrhea or stomach cramps
•
dizziness, fainting, or “passing out” (unconsciousness)

2.
Always carry your EpiPen or EpiPen Jr with you because you may not know when anaphylaxis may happen.
Talk to your healthcare provider if you need additional units to keep at work, school, or other locations. Tell your family members, caregivers, and others where you keep your EpiPen or EpiPen Jr and how to use it before you need it. You may be unable to speak in an allergic emergency.
3.
When you have an allergic emergency (anaphylaxis)

•
Use the EpiPen or EpiPen Jr right away.
•
Get emergency medical help right away. You may need further medical attention. You may need to use a second EpiPen or EpiPen Jr if symptoms continue or recur. Only a healthcare provider should give additional doses of epinephrine if you need more than 2 injections for a single anaphylaxis episode.

What are EpiPen and EpiPen Jr?

•
EpiPen and EpiPen Jr are disposable, prefilled automatic injection devices (auto-injectors) used to treat life-threatening, allergic emergencies including anaphylaxis in people who are at risk for or have a history of serious allergic emergencies. Each device contains a single dose of epinephrine.
•
EpiPen and EpiPen Jr are for immediate self (or caregiver) administration and do not take the place of emergency medical care. You should get emergency help right away after using EpiPen and EpiPen Jr.
•
EpiPen and EpiPen Jr are for people who have been prescribed this medicine by their healthcare provider.
•
The EpiPen Auto-Injector (0.3 mg) is for patients who weigh 66 pounds or more (30 kilograms or more).
•
The EpiPen Jr Auto-Injector (0.15 mg) is for patients who weigh about 33 to 66 pounds (15 to 30 kilograms).
•
It is not known if EpiPen and EpiPen Jr are safe and effective in children who weigh less than 33 pounds (15 kilograms).

What should I tell my healthcare provider before using the EpiPen or EpiPen Jr?

Before you use EpiPen or EpiPen Jr, tell your healthcare provider about all your medical conditions, but especially if you:

•
have heart problems or high blood pressure
•
have diabetes
•
have thyroid problems
•
have asthma
•
have a history of depression
•
have Parkinson’s disease
•
have any other medical conditions
•
are pregnant or plan to become pregnant. It is not known if epinephrine will harm your unborn baby.
•
are breastfeeding or plan to breastfeed. It is not known if epinephrine passes into your breast milk.

Tell your healthcare provider about all the medicines you take, including prescription and over-the-counter medicines, vitamins, and herbal supplements. Tell your healthcare provider of all known allergies.

Especially tell your healthcare provider if you take certain asthma medicines.

EpiPen or EpiPen Jr and other medicines may affect each other, causing side effects. EpiPen or EpiPen Jr may affect the way other medicines work, and other medicines may affect how EpiPen or EpiPen Jr works.

Know the medicines you take. Keep a list of them to show your healthcare provider and pharmacist when you get a new medicine.

Use your EpiPen or EpiPen Jr for treatment of anaphylaxis as prescribed by your healthcare provider, regardless of your medical conditions or the medicines you take.

How should I use EpiPen and EpiPen Jr?

•
Each EpiPen or EpiPen Jr Auto-Injector contains only 1 dose of medicine.
•
EpiPen or EpiPen Jr should be injected into the middle of your outer thigh (upper leg). It can be injected through your clothing if needed.
•
Read the Instructions for Use at the end of this Patient Information Leaflet about the right way to use EpiPen and EpiPen Jr.
•
Your healthcare provider will show you how to safely use the EpiPen or EpiPen Jr Auto-Injector.
•
Use your EpiPen or EpiPen Jr exactly as your healthcare provider tells you to use it. You may need to use a second EpiPen or EpiPen Jr if symptoms continue or recur. Only a healthcare provider should give additional doses of epinephrine if you need more than 2 injections for a single anaphylaxis episode.
•
Caution: Never put your thumb, fingers, or hand over the orange tip. Never press or push the orange tip with your thumb, fingers, or hand. The needle comes out of the orange tip. Accidental injection into finger, hands or feet may cause a loss of blood flow to these areas. If this happens, go immediately to the nearest emergency room. Tell the healthcare provider where on your body you received the accidental injection.
•
Your EpiPen and EpiPen Jr Auto-Injector may come packaged with an EpiPen Trainer and separate Trainer Instructions for Use. The EpiPen Trainer has a grey color. The grey EpiPen Trainer contains no medicine and no needle. Periodically practice with your EpiPen Trainer before an allergic emergency happens to make sure you are able to safely use the real EpiPen and EpiPen Jr Auto-Injector in an emergency. Always carry your real EpiPen or EpiPen Jr Auto-Injector with you in case of an allergic emergency. Additional training resources are available at www.epipen.com.
•
Do not drop the carrier tube or auto-injector. If the carrier tube or auto-injector is dropped, check for damage and leakage. Dispose of the auto-injector and carrier tube, and replace if damage or leakage is noticed or suspected.

What are the possible side effects of the EpiPen and EpiPen Jr?

EpiPen and EpiPen Jr may cause serious side effects.

•
The EpiPen or EpiPen Jr should only be injected into the middle of your outer thigh (upper leg).Do not inject the EpiPen or EpiPen Jr into your:

•
veins
•
buttocks
•
fingers, toes, hands, or feet

If you accidentally inject EpiPen or EpiPen Jr into any other part of your body, go to the nearest emergency room right away. Tell the healthcare provider where on your body you received the accidental injection.
•
Rarely, patients who have used EpiPen or EpiPen Jr may develop infections at the injection site within a few days of an injection. Some of these infections can be serious. Call your healthcare provider right away if you have any of the following at an injection site:

•
redness that does not go away
•
swelling
•
tenderness
•
the area feels warm to the touch

•
Cuts on the skin, bent needles, and needles that remain in the skin after the injection, have happened in young children who do not cooperate and kick or move during an injection. If you inject a young child with EpiPen or EpiPen Jr, hold their leg firmly in place before and during the injection to prevent injuries. Ask your healthcare provider to show you how to properly hold the leg of a young child during injection.
•
If you have certain medical conditions, or take certain medicines, your condition may get worse or you may have longer lasting side effects when you use your EpiPen or EpiPen Jr. Talk to your healthcare provider about all your medical conditions.

Common side effects of EpiPen and EpiPen Jr include:

•
fast, irregular or “pounding” heartbeat
•
sweating
•
headache
•
weakness
•
shakiness
•
paleness
•
feelings of over excitement, nervousness or anxiety
•
dizziness
•
nausea or vomiting
•
breathing problems

These side effects may go away with rest. Tell your healthcare provider if you have any side effect that bothers you or that does not go away.

These are not all the possible side effects of the EpiPen or EpiPen Jr. For more information, ask your healthcare provider or pharmacist.

Call your healthcare provider for medical advice about side effects. You may report side effects to FDA at 1-800-FDA-1088.

How should I store EpiPen and EpiPen Jr?

•
Store EpiPen and EpiPen Jr at room temperature between 68° to 77° F (20° to 25° C).
•
Protect from light.
•
Do not expose to extreme cold or heat. For example, do not store in your vehicle’s glove box and do not store in the refrigerator or freezer.
•
Examine the contents in the clear window of your auto-injector periodically. The solution should be clear. If the solution is discolored (pinkish or brown color) or contains solid particles, replace the unit.
•
Always keep your EpiPen or EpiPen Jr Auto-Injector in the carrier tube to protect it from damage; however, the carrier tube is not waterproof.
•
The blue safety release helps to prevent accidental injection. Keep the blue safety release on until you need to use EpiPen or EpiPen Jr.
•
Your EpiPen or EpiPen Jr has an expiration date. Replace it before the expiration date.

Keep EpiPen and EpiPen Jr and all medicines out of the reach of children.

General information about the safe and effective use of EpiPen and EpiPen Jr

Medicines are sometimes prescribed for purposes other than those listed in a Patient Information Leaflet. Do not use the EpiPen or EpiPen Jr for a condition for which it was not prescribed. Do not give your EpiPen or EpiPen Jr to other people.

This Patient Information Leaflet summarizes the most important information about EpiPen and EpiPen Jr. If you would like more information, talk to your healthcare provider. You can ask your pharmacist or healthcare provider for information about EpiPen and EpiPen Jr that is written for health professionals.

For more information and video instructions on the use of EpiPen and EpiPen Jr, go to www.epipen.com or call 1-800-395-3376.

What are the ingredients in EpiPen and EpiPen Jr?

Active Ingredients: Epinephrine
Inactive Ingredients: sodium chloride, sodium metabisulfite, hydrochloric acid, and water.

Important Information

•
The EpiPen Auto-Injector has a yellow colored label.
•
The EpiPen Jr Auto-Injector has a green colored label.
•
The EpiPen Trainer has a grey color and contains no medicine and no needle.
•
Your auto-injector is designed to work through clothing.
•
The blue safety release on the EpiPen and EpiPen Jr Auto-Injector helps to prevent accidental injection of the device. Do not remove the blue safety release until you are ready to use it.
•
Only inject into the middle of the outer thigh (upper leg). Never inject into any other part of the body.
•
Never put your thumb, fingers, or your hand over the orange tip. The needle comes out of the orange tip.
•
If an accidental injection happens, get medical help right away.
•
Do not place patient information or any other foreign objects in the carrier tube with the Auto-Injector, as this may prevent you from removing the Auto-Injector for use.

Instructions for Use

EPIPEN®
(epinephrine injection, USP) Auto-Injector 0.3 mg
EpiPen® = one dose of 0.3 mg epinephrine, USP 0.3 mg/0.3 mL

EPIPEN JR®
(epinephrine injection, USP) Auto-Injector 0.15 mg
EpiPen Jr® = one dose of 0.15 mg epinephrine, USP 0.15 mg/0.3 mL

For allergic emergencies (anaphylaxis)

Read these Instructions for Use carefully before you use EpiPen or EpiPen Jr. Before you need to use your EpiPen or EpiPen Jr, make sure your healthcare provider shows you the right way to use it. Parents, caregivers, and others who may be in a position to administer EpiPen or EpiPen Jr Auto-Injector should also understand how to use it as well. If you have any questions, ask your healthcare provider.

Your EpiPen and EpiPen Jr Auto-Injector

A dose of EpiPen or EpiPen Jr® requires 3 simple steps: Prepare, Administer and Get emergency medical help

Step 1. Prepare EpiPen or EpiPen Jr for injection

Note:

•
The needle comes out of the orange tip.
•
To avoid an accidental injection, never put your thumb, fingers or hand over the orange tip. If an accidental injection happens, get medical help right away.

Step 2. Administer EpiPen or EpiPen Jr

Step 3. Get emergency medical help now. You may need further medical attention. You may need to use a second EpiPen or EpiPen Jr Auto-Injector if symptoms continue or recur.

•
Take your used auto-injector with you when you go to see a healthcare provider.
•
Tell the healthcare provider that you have received an injection of epinephrine. Show the healthcare provider where you received the injection.
•
Give your used EpiPen or EpiPen Jr Auto-Injector to the healthcare provider for inspection and proper disposal.
•
Ask for a refill, if needed.

Note:

•
The used auto-injector with extended needle cover will not fit in the carrier tube.
•
EpiPen and EpiPen Jr are single-use injectable devices that deliver a fixed dose of epinephrine. The auto-injector cannot be reused. Do not attempt to reuse EpiPen after the device has been activated. It is normal for most of the medicine to remain in the auto-injector after the dose is injected. The correct dose has been administered if the orange needle tip is extended and the window is blocked.
•
Your EpiPen and EpiPen Jr Auto-Injector may come packaged with an EpiPen Trainer and separate Trainer Instructions for Use. The EpiPen Trainer has a grey color. The grey EpiPen Trainer contains no medicine and no needle. Practice with your EpiPen Trainer, but always carry your real EpiPen or EpiPen Jr Auto-Injector in case of an allergic emergency.
•
If you are administering EpiPen or EpiPen Jr to a young child, ask your healthcare provider to show you how to properly hold the leg in place while administering a dose.
•
Do not try to take the EpiPen or EpiPen Jr Auto-Injector apart.

This Patient Information and Instructions for Use has been approved by the U.S. Food and Drug Administration.

Manufactured for:

Mylan Specialty L.P., Morgantown, WV 26505, U.S.A. by Meridian Medical Technologies, Inc., Columbia, MD 21046, U.S.A., a Pfizer company

EpiPen® and EpiPen Jr® are registered trademarks of Mylan Inc. licensed exclusively to its wholly-owned affiliate, Mylan Specialty L.P. of, Morgantown, WV 26505, U.S.A.

Copyright © 2017 Meridian Medical Technologies. All rights reserved.

Revised: 2/2017
MS:PIL:EPI:R3
0001984

EPIPEN®
(epinephrine injection, USP) Auto-Injector 0.3 mg
EpiPen® = one dose of 0.3 mg epinephrine, USP 0.3 mg/0.3 mL

EPIPEN JR®
(epinephrine injection, USP) Auto-Injector 0.15 mg
EpiPen Jr® = one dose of 0.15 mg epinephrine, USP 0.15 mg/0.3 mL

MyEpiPen.com

Register your EpiPen or EpiPen Jr Auto-Injector at MyEpiPen.com and find out more about:

•
Free EpiPen Auto-Injector Refill Reminder Program. It is important to keep your auto-injector up-to-date.

Register up to 6 EpiPen or EpiPen Jr Auto- Injectors and receive automatic Refill Reminder Alerts.

•
Receive periodic information related to allergies and allergens.
•
Instructional Video

For more information about EpiPen or EpiPen Jr Auto-Injectors and proper use of the product, call Mylan at 1-877-446-3679 or visit www.epipen.com.

EpiPen Trainer Instructions for Use

In an emergency: Do not use the grey Trainer. Use your real yellow EpiPen® or green EpiPen Jr® Auto-Injector.

Important Information

•
The Trainer label has a grey color.
•
The Trainer contains no medicine and no needle.
•
Periodically practice with the grey colored Trainer before an allergic emergency (anaphylaxis) happens to make sure you are able to safely use the real yellow EpiPen or green EpiPen Jr Auto-Injector in case of an emergency.
•
Always carry your real yellow EpiPen or green EpiPen Jr Auto-Injector in case of an allergic emergency.

The EpiPen Trainer

Familiarize yourself with this grey Trainer. Practice until you are comfortable using it.

Your grey colored Trainer:

•
Never put your thumb, other fingers, or hand over the Orange Tip.
•
The Orange Tip is where the needle comes out of your EpiPen or EpiPen Jr Auto-Injector.

Note: With the real yellow EpiPen or green EpiPen Jr Auto-Injector, the orange tip covers the needle after self-injection to help protect you from accidentally sticking yourself or others.

Practice Session Information

In case of an allergic emergency, use the real yellow EpiPen or green EpiPen Jr Auto-Injector and not the grey Trainer.

Follow instructions above. Repeat as often as needed until you are able to self-inject quickly and correctly.

Reread:

•
These Trainer Instructions for Use
•
The “Patient Information” that comes with your EpiPen or EpiPen Jr Auto-Injector

Train others who could help you in an emergency:

•
Your parents, caregivers, and others who may be in a position to administer EpiPen or EpiPen Jr should know how to help you during an allergic emergency (anaphylaxis). Before an emergency occurs, have them:

•
Practice activating the Trainer
•
Read these Trainer Instructions and the “Patient Information”

For more information about the EpiPen and EpiPen Jr Auto-Injector and the proper use of the products, go to www.epipen.com.

Caution:

Important differences between the Trainer and your real yellow EpiPen or green EpiPen Jr Auto-Injector

This Trainer Instructions for Use has been approved by the U.S. Food and Drug Administration.

Manufactured for Mylan Specialty L.P., Morgantown, WV 26505, U.S.A. by Meridian Medical Technologies, Inc., Columbia, MD 21046, U.S.A., a Pfizer company

EpiPen® and EpiPen Jr® are registered trademarks of Mylan Inc. licensed exclusively to its wholly-owned affiliate, Mylan Specialty L. P. of Morgantown, WV 26505, U.S.A.

Copyright © 2017 Meridian Medical Technologies. All rights reserved.

Revised: 2/2017
MS:EPIT:R4
0001994

PRINCIPAL DISPLAY PANEL, YELLOW PEN 0.3mg

Rx only

For Allergic Emergencies (Anaphylaxis)

(epinephrine injection, USP)
Auto-Injectors 0.3 mg

Never put thumb, fingers or hand over orange tip.
Do not remove blue safety release until ready to use.

Each EpiPen®Auto-Injector delivers one 0.3 mg intramuscular dose
of epinephrine from epinephrine injection, USP 0.3 mg/0.3mL.

Discard unit after use. The Trainer contains no medicine and no needle.

Read enclosed patient package insert carefully before using.

See enclosed Patient Information
Leaflet for complete instructions for use.

Note: The needle comes out of the orange tip.

Never put your thumb, fingers or hand
over the orange tip.

Register your EpiPen® Auto-Injectors at www.epipen.com
to receive free refill reminders

Replace if discolored. Store at 68º to 77ºF
(20º to 25ºC). Do not refrigerate.

Protect from light.

Manufactured for Mylan Specialty L.P., Morgantown, WV 26505, USA
by Meridian Medical Technologies, Inc.,
Columbia, MD 21046, USA, a Pfizer company

EpiPen® and EpiPen Jr® are registered trademarks of
Mylan Inc. licensed exclusively to its wholly-owned
affiliate, Mylan Specialty L.P. of Morgantown, WV 26505, USA

Copyright © 2017 Meridian Medical Technologies. All rights reserved.

MS:50002:2C:R3

PRINCIPAL DISPLAY PANEL, GREEN 0.15mg

Rx only

For Allergic Emergencies (Anaphylaxis)

(epinephrine injection, USP)
Auto-Injectors 0.15 mg

Never put thumb, fingers or hand over orange tip.
Do not remove blue safety release until ready to use.

Each EpiPen Jr®Auto-Injector delivers one 0.15 mg intramuscular dose
of epinephrine from epinephrine injection, USP 0.15 mg/0.3 mL.

Discard unit after use. The Trainer contains no medicine and no needle.

Read enclosed patient package insert carefully before using.

See enclosed Patient Information
Leaflet for complete instructions for use.

Note: The needle comes out of the orange tip.

Never put your thumb, fingers or hand
over the orange tip.

Register your EpiPen Jr® Auto-Injectors at www.epipen.com
to receive free refill reminders

Replace if discolored. Store at 68º to 77ºF
(20º to 25ºC). Do not refrigerate.

Protect from light.

Manufactured for Mylan Specialty L.P., Morgantown, WV 26505, USA
by Meridian Medical Technologies, Inc.,
Columbia, MD 21046, USA, a Pfizer company

EpiPen® and EpiPen Jr® are registered trademarks of
Mylan Inc. licensed exclusively to its wholly-owned
affiliate, Mylan Specialty L.P. of Morgantown, WV 26505, USA

Copyright © 2017 Meridian Medical Technologies. All rights reserved.

MS:50102:2C:R3